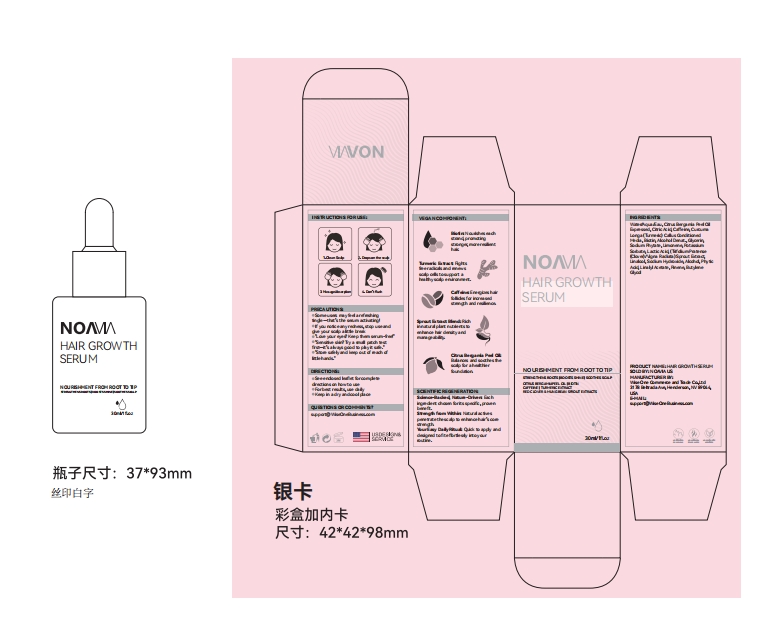 DRUG LABEL: NOAVIA HAIR GROWTH SERUM
NDC: 85212-0014 | Form: LIQUID
Manufacturer: Beijing JUNGE Technology Co., Ltd.
Category: otc | Type: HUMAN OTC DRUG LABEL
Date: 20250227

ACTIVE INGREDIENTS: ZINGIBER OFFICINALE (GINGER) ROOT OIL 2 g/100 mL; PANAX GINSENG ROOT 5 g/100 mL
INACTIVE INGREDIENTS: 1,2-HEXANEDIOL 0.5 mL/100 mL; TRITICUM AESTIVUM WHOLE 1 mL/100 mL; COFFEA ARABICA WHOLE 0.5 mL/100 mL; CAPRYLHYDROXAMIC ACID 0.1 mL/100 mL; NIACINAMIDE 1 mL/100 mL; GLYCERYL CAPRYLATE 0.1 mL/100 mL; CORDYCEPS MILITARIS WHOLE 5 mL/100 mL; TYPHA ORIENTALIS WHOLE 1 mL/100 mL; BUTYLENE GLYCOL 5 mL/100 mL; PANICUM MILIACEUM WHOLE 1 mL/100 mL; DIPROPYLENE GLYCOL 0.1 mL/100 mL; FORSYTHIA SUSPENSA FRUIT 2 mL/100 mL; AQUA 73.7 mL/100 mL; SOPHORA FLAVESCENS ROOT 2 mL/100 mL

DOSAGE AND ADMINISTRATION

30ml (1fl.oz)

INDICATIONS AND USAGE

1、Cleanse your scalp before use
2、Apply the serum evenly to the scalp
3、Massage gently into the scalp to promote absorption
4、Finish by brushing your hair as usual and don't rinse it out

PRECAUTIONS

Some users may feel a refreshing tingle—that’s the serum activating!
If you notice any redness, stop use and give your scalp a little break
"Love your eyes? Keep them serum-free!"
"Sensitive skin? Try a small patch test first—it’s always good to play it safe."
"Store safely and keep out of reach of little hands.

ACTIVE INGREDIENT

PANAX GINSENG ROOT EXTRACT
ZINGIBER OFFICINALE (GINGER) ROOT EXTRACT

INACTIVE INGREDIENT

AQUA
BUTYLENE GLYCOL
CORDYCEPS MILITARIS EXTRACT
FORSYTHIA SUSPENSA FRUIT EXTRACT
SOPHORA FLAVESCENS ROOT EXTRACT
TRITICUM AESTIVUM (WHEAT) SEED EXTRACT
TYPHA ORIENTALIS EXTRACT
PANICUM MILIACEUM (MILLET) SEED EXTRACT
NIACINAMIDE
KOHHII EKISU
BIOTIN/FOLIC ACID/CYANOCOBALAMIN/NIACINAMIDE/PANTOTHENIC ACID/PYRIDOXINE/RIBOFLAVIN/THIAMINE/YEAST POLYPEPTIDES
1,2-HEXANEDIOL
PROPYLENE GLYCOL
GLYCERYL CAPRYLATE
CAPRYLHYDROXAMIC ACID

PURPOSE

Improves Scalp Environment
Promotes Hair Growth

KEEP OUT OF REACH OF CHILDREN

swallowed, get medical help or contact a Poison Control Center rightaway.

WARNINGS

For External Use Only.
Avoid Direct Contact with Eyes.
If the product gets into your eyes, rinse immediately with plenty of water.
Discontinue Use if Irritation Occurs.

Keep Out of Reach of Children.